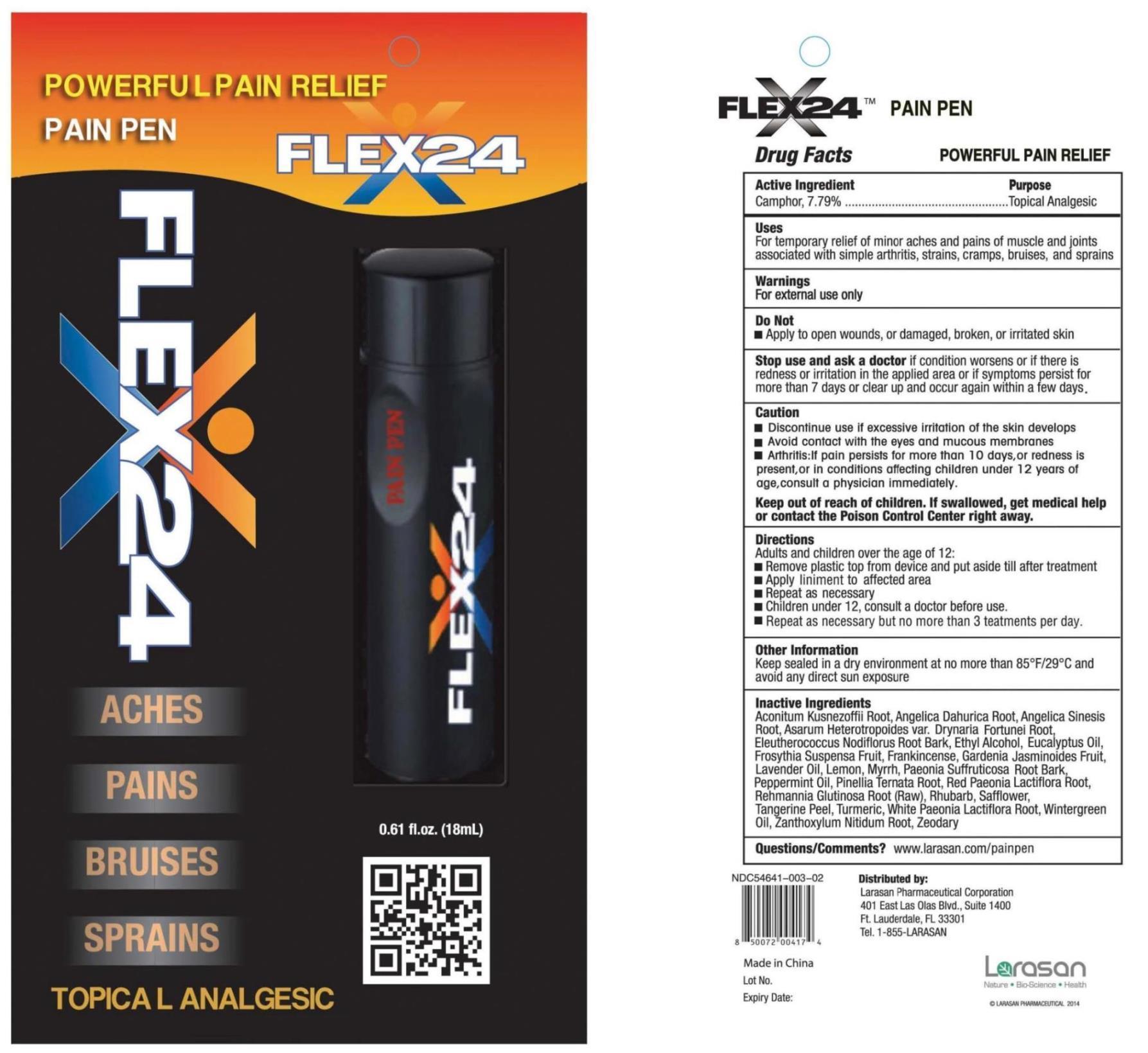 DRUG LABEL: Flex24 Pain Pen
NDC: 54641-003 | Form: LIQUID
Manufacturer: Larasan Pharmaceutical Corporation
Category: otc | Type: HUMAN OTC DRUG LABEL
Date: 20191208

ACTIVE INGREDIENTS: CAMPHOR (NATURAL) 7.79 g/100 mL
INACTIVE INGREDIENTS: ACONITUM KUSNEZOFFII ROOT; ANGELICA DAHURICA ROOT; ANGELICA SINENSIS ROOT; DRYNARIA FORTUNEI ROOT; ELEUTHEROCOCCUS NODIFLORUS ROOT BARK; ALCOHOL; EUCALYPTUS OIL; FORSYTHIA SUSPENSA FRUIT; FRANKINCENSE; GARDENIA JASMINOIDES FRUIT; LAVENDER OIL; LEMON; MYRRH; PAEONIA SUFFRUTICOSA ROOT BARK; PEPPERMINT OIL; PINELLIA TERNATA ROOT; PAEONIA LACTIFLORA ROOT; REHMANNIA GLUTINOSA ROOT; RHUBARB; SAFFLOWER; TANGERINE PEEL; TURMERIC; METHYL SALICYLATE; ZANTHOXYLUM NITIDUM ROOT; ZEDOARY

Active Ingredient

Camphor, 7.79%

Purpose

Topical analgesic

Uses

For temporary relief of minor aches and pains of muscle and joints associated with simple arthritis, strains, cramps, bruises, and sprains

Warnings

For external use only

Do not

• Apply to open wounds, or damaged, broken, or irritated skin

Stop use and ask a doctor

if condition worsens or if there is redness or irritation in the applied area or if symptoms persist for more than 7 days or clear up and occur again within a few days.

Caution

• Discontinue use if excessive irritation of the skin develops
• Avoid contact with the eyes and mucous membranes
• Arthritis: If pain persists for more than 10 days, or redness is present, or in conditions affecting children under 12 years of age, consult a physician immediately.

Keep out of reach of children

If swallowed, get medical help or contact a Poison Control Center right away

Directions

Adults and children over the age of 12:

• Remove plastic top from device and put aside till after treatment

• Apply liniment to affected area

• Repeat as necessary but no more than 3 treatments per day

• Children under 12, consult a doctor before use.

Other Information

Keep sealed in a dry environment at no more than 85°F/29°C and avoid any direct sun exposure

Inactive Ingredients

Aconitum Kusnezoffii Root, Angelica Dahurica Root, Angelica Sinesis Root, Asarum Heterotropoides var. Drynaria Fortunei Root, Eleutherococcus Nodiflorus Root Bark, Ethyl Alcohol, Eucalyptus Oil, Frosythia Suspensa Fruit, Frankincense, Gardenia Jasminoides Fruit, Lavender Oil, Lemon, Myrrh, Paeonia Suffruticosa Root Bark, Peppermint Oil, Pinellia Ternata Root, Red Paeonia Lactiflora Root, Rehmannia Glutinosa Root (Raw), Rhubarb, Safflower, Tangerine Peel, Turmeric, White Paeonia Lactiflora Root, Wintergreen Oil, Zanthoxylum Nitidum Root, Zeodary

Questions/Comments?

www.larasan.com/painpen

Flex24™ Pain Pen

Powerful Pain Relief

Distributed by: Larasan Pharmaceutical Corporation, 401 East Las Olas Blvd., Suite 1400, Ft. Lauderdale, FL 33301

Tel. 1-855-LARASAN

NDC 54641-003-02

Made in Chinda

Lot No.:

Expiry Date:

Larasan

Nature Bioscience Health

© Larasan Pharmaceutical 2014

Flex24™ Pain Pen

Powerful Pain Relief

Aches Pains Bruises Sprains

Topical Analgesic

0.61 fl. oz. (18 mL)